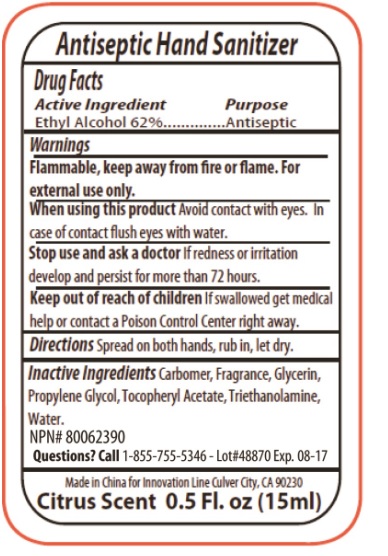 DRUG LABEL: 5253 hand sanitizer
NDC: 76138-117 | Form: GEL
Manufacturer: Innovation Specialties
Category: otc | Type: HUMAN OTC DRUG LABEL
Date: 20240710

ACTIVE INGREDIENTS: ALCOHOL 62 mL/100 mL
INACTIVE INGREDIENTS: CARBOMER HOMOPOLYMER, UNSPECIFIED TYPE; GLYCERIN; PROPYLENE GLYCOL; .ALPHA.-TOCOPHEROL ACETATE; TROLAMINE; WATER

5253 hand sanitizer

Active Ingredient

Ethyl Alcohol 62%

Purpose

Antiseptic

Uses

Hand sanitizer to help decrease bacteria on the skin.

Warnings

Flammable, keep away from fire or flame. For external use only.

When using this productAvoid contact with eyes. In case of contact flush eyes with water.

Stop use and ask a doctorIf redness or irritation develop and persist for more than 72 hours.

Keep out of reach of children.If swallowed get medical help or contact a Poison Control Center right away.

Directions

Spread on both hands, rub in, let dry.

Inactive Ingredients

Carbomer, Fragrance, Glycerin, Propylene Glycol, Tocopheryl Acetate, Triethanolamine, Water.

Questions?

Call 1-855-755 5346

NPN # 80062390

Made in China For Innovation Line Culver City, CA 90230

Citrus Scent